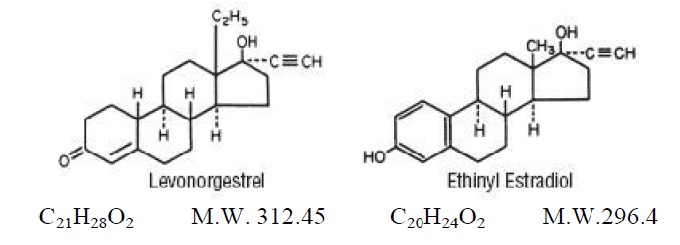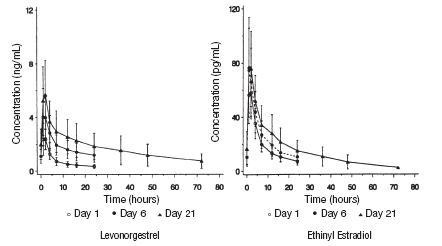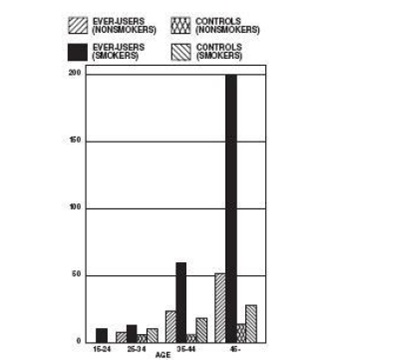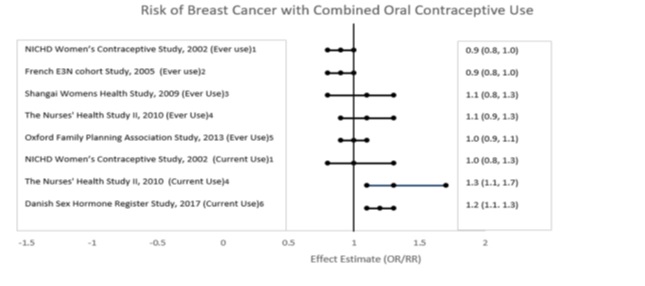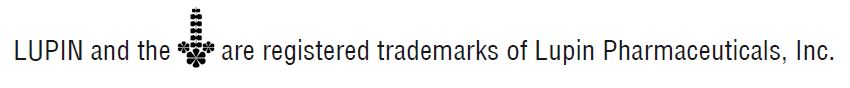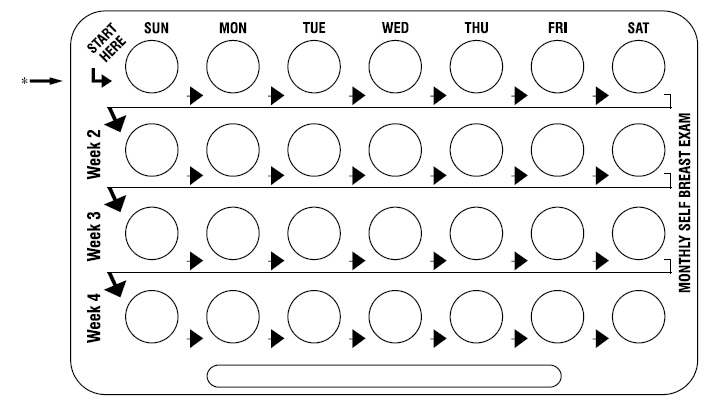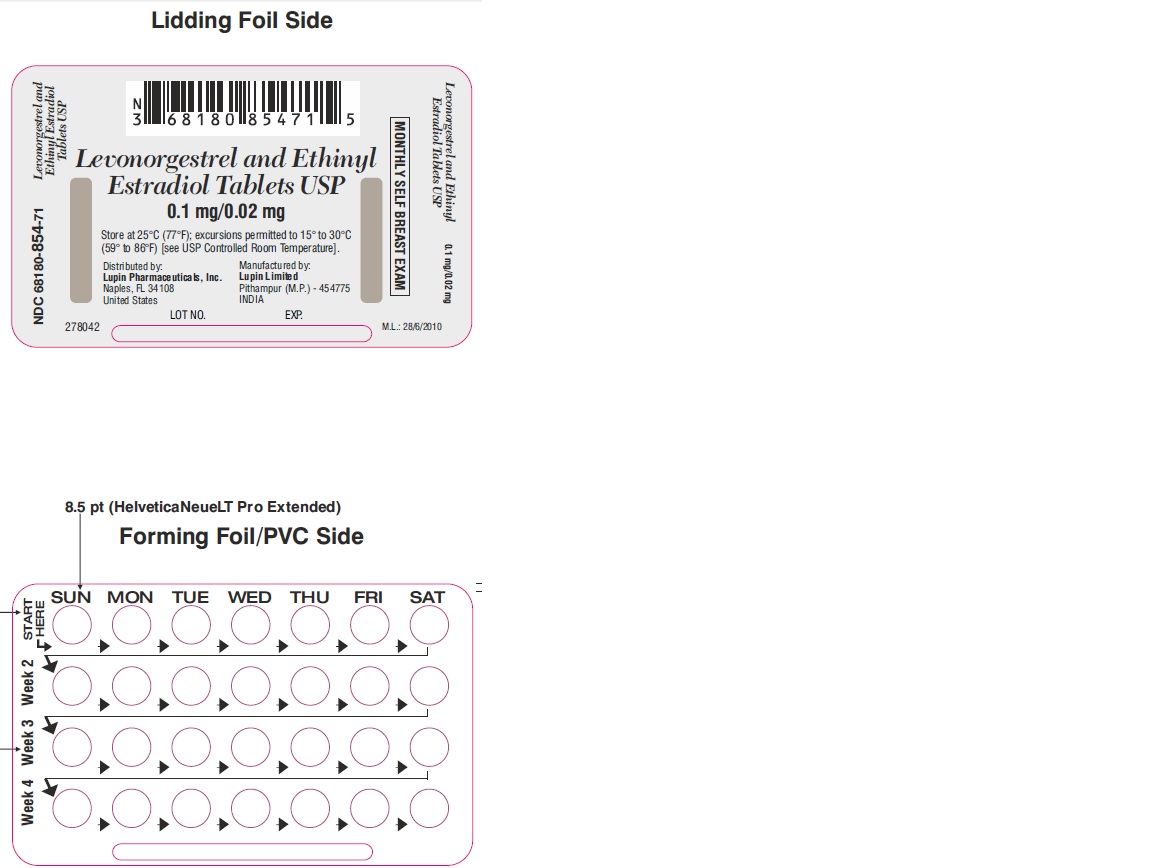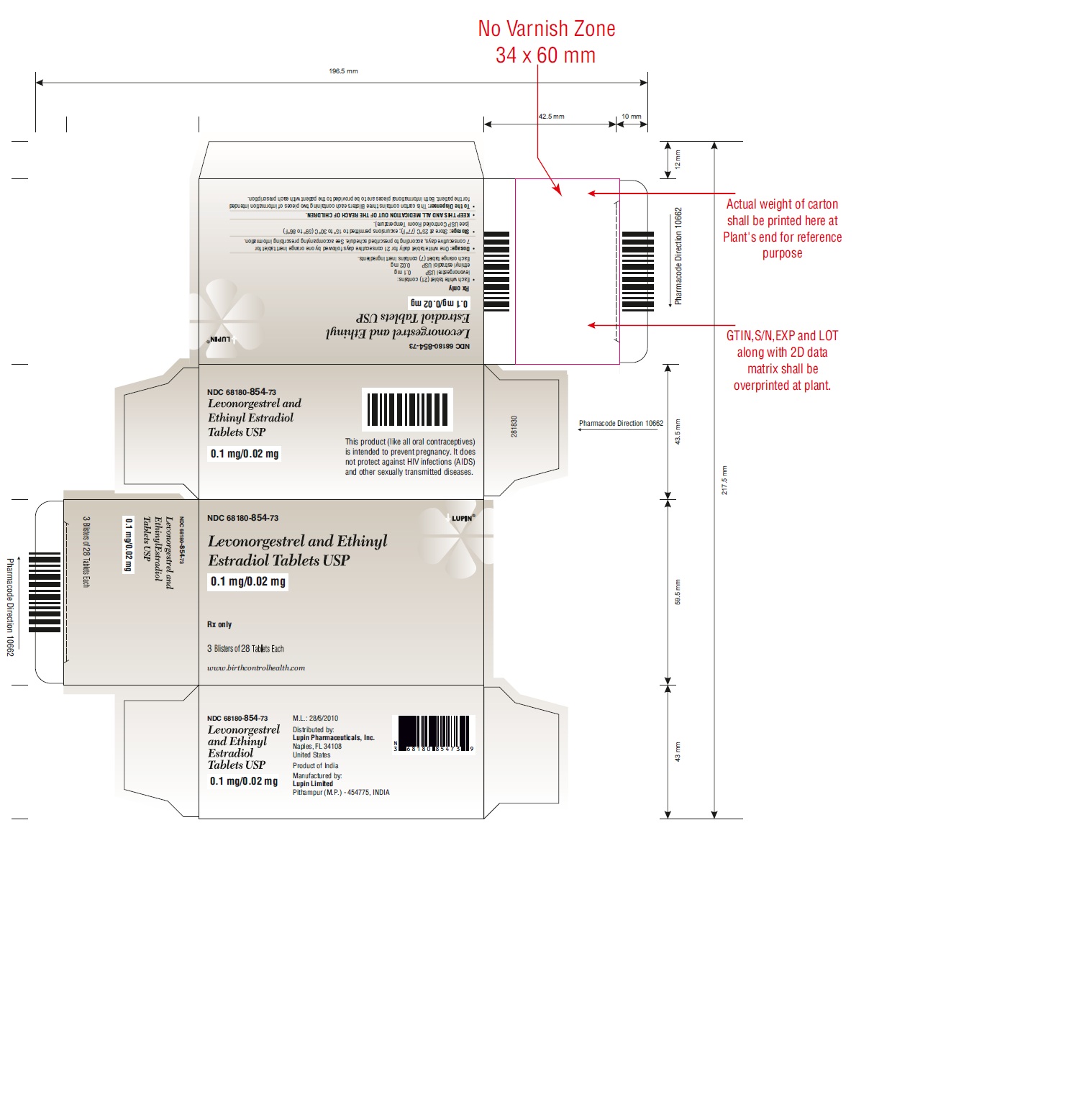 DRUG LABEL: Levonorgestrel and Ethinyl Estradiol

NDC: 68180-854 | Form: KIT | Route: ORAL
Manufacturer: Lupin Pharmaceuticals, Inc.
Category: prescription | Type: HUMAN PRESCRIPTION DRUG LABEL
Date: 20251209

ACTIVE INGREDIENTS: ETHINYL ESTRADIOL 0.02 mg/1 1; LEVONORGESTREL 0.1 mg/1 1
INACTIVE INGREDIENTS: CROSCARMELLOSE SODIUM; LACTOSE MONOHYDRATE; MAGNESIUM STEARATE; CELLULOSE, MICROCRYSTALLINE; POVIDONE; CROSCARMELLOSE SODIUM; FD&C YELLOW NO. 6; LACTOSE MONOHYDRATE; MAGNESIUM STEARATE; CELLULOSE, MICROCRYSTALLINE

Levonorgestrel and Ethinyl Estradiol Tablets USP, 0.1 mg/0.02 mg

Rx only

Patients should be counseled that oral contraceptives do not protect against transmission of HIV (AIDS) and other sexually transmitted diseases (STDs) such as chlamydia, genital herpes, genital warts, gonorrhea, hepatitis B, and syphilis.

DESCRIPTION

Each active, white tablet (21) contains 0.1 mg of levonorgestrel, d(-)-13β- ethyl-17α-ethinyl-17β-hydroxygon-4-en-3-one, a totally synthetic progestogen, and 0.02 mg of ethinyl estradiol, 17α-ethinyl-1,3,5(10)-estratriene-3, 17β-diol. The inactive ingredients present are croscarmellose sodium, lactose monohydrate, magnesium stearate, microcrystalline cellulose and povidone.

Each inert, orange tablet (7) contains the following inactive ingredients: croscarmellose sodium, FD&C Yellow #6, lactose monohydrate, magnesium stearate, and microcrystalline cellulose.

CLINICAL PHARMACOLOGY

Mode of Action

Combination oral contraceptives act by suppression of gonadotropins. Although the primary mechanism of this action is inhibition of ovulation, other alterations include changes in the cervical mucus (which increase the difficulty of sperm entry into the uterus) and the endometrium (which reduce the likelihood of implantation).

PHARMACOKINETICS

Absorption

No specific investigation of the absolute bioavailability of levonorgestrel and ethinyl estradiol in humans has been conducted. However, literature indicates that levonorgestrel is rapidly and completely absorbed after oral administration (bioavailability about 100%) and is not subject to first-pass metabolism. Ethinyl estradiol is rapidly and almost completely absorbed from the gastrointestinal tract but, due to first-pass metabolism in gut mucosa and liver, the bioavailability of ethinyl estradiol is between 38% and 48%.

After a single dose of levonorgestrel and ethinyl estradiol tablets to 22 women under fasting conditions, maximum serum concentrations of levonorgestrel are 2.8 ± 0.9 ng/mL (mean ± SD) at 1.6 ± 0.9 hours. At steady state, attained from day 19 onwards, maximum levonorgestrel concentrations of 6.0 ± 2.7 ng/mL are reached at 1.5 ± 0.5 hours after the daily dose. The minimum serum levels of levonorgestrel at steady state are 1.9 ± 1.0 ng/mL. Observed levonorgestrel concentrations increased from day 1 (single dose) to days 6 and 21 (multiple doses) by 34% and 96%, respectively (Figure 1).

Unbound levonorgestrel concentrations increased from day 1 to days 6 and 21 by 25% and 83%, respectively. The kinetics of total levonorgestrel are non-linear due to an increase in binding of levonorgestrel to sex hormone binding globulin (SHBG), which is attributed to increased SHBG levels that are induced by the daily administration of ethinyl estradiol.

Following a single dose, maximum serum concentrations of ethinyl estradiol of 62 ± 21 pg/mL are reached at 1.5 ± 0.5 hours. At steady state, attained from at least day 6 onwards, maximum concentrations of ethinyl estradiol were 77 ± 30 pg/mL and were reached at 1.3 ± 0.7 hours after the daily dose. The minimum serum levels of ethinyl estradiol at steady state are 10.5 ± 5.1 pg/mL. Ethinyl estradiol concentrations did not increase from days 1 to 6, but did increase by 19% from days 1 to 21 (FIGURE I).

FIGURE I: Mean (SE) levonorgestrel and ethinyl estradiol serum concentrations in 22 subjects receiving levonorgestrel and ethinyl estradiol tablets (100 mcg levonorgestrel and 20 mcg ethinyl estradiol)

TABLE I provides a summary of levonorgestrel and ethinyl estradiol pharmacokinetic parameters.

TABLE I: MEAN (SD) PHARMACOKINETIC PARAMETERS OF LEVONORGESTREL and ETHINYL ESTRADIOL TABLETS OVER A 21-DAY DOSING PERIOD
Header$ Levonorgestrel
 | Cmax | Tmax | AUC | CL/F | Vλz/F | SHBG
Day | ng/mL | h | ng•h/mL | mL/h/kg | L/kg | nmol/L
1 | 2.75 (0.88) | 1.6 (0.9) | 35.2 (12.8) | 53.7 (20.8) | 2.66 (1.09) | 57 (18)
6 | 4.52 (1.79) | 1.5 (0.7) | 46.0 (18.8) | 40.8(14.5) | 2.05 (0.86) | 81 (25)
21 | 6.00 (2.65) | 1.5 (0.5) | 68.3 (32.5) | 28.4 (10.3) | 1.43 (0.62) | 93 (40)
Unbound Levonorgestrel
 | pg/mL | h | pg•h/mL | L/h/kg | L/kg | fu%
1 | 51.2 (12.9) | 1.6 (0.9) | 654 (201) | 2.79 (0.97) | 135.9 (41.8) | 1.92 (0.30)
6 | 77.9 (22.0) | 1.5 (0.7) | 794 (240) | 2.24 (0.59) | 112.4 (40.5) | 1.80 (0.24)
21 | 103.6 (36.9) | 1.5 (0.5) | 1177 (452) | 1.57 (0.49) | 78.6 (29.7) | 1.78 (0.19)
Ethinyl Estradiol
 | pg/mL | h | pg•h/mL | mL/h/kg | L/kg
1 | 62.0 (20.5) | 1.5 (0.5) | 653 (227) | 567 (204) | 14.3 (3.7)
6 | 76.7 (29.9) | 1.3 (0.7) | 604 (231) | 610 (196) | 15.5 (4.0)
21 | 82.3 (33.2) | 1.4 (0.6) | 776 (308) | 486 (179) | 12.4 (4.1)

Distribution

Levonorgestrel in serum is primarily bound to SHBG. Ethinyl estradiol is about 97% bound to plasma albumin. Ethinyl estradiol does not bind to SHBG, but induces SHBG synthesis.

Metabolism

Levonorgestrel: The most important metabolic pathway occurs in the reduction of the Δ4-3-oxo group and hydroxylation at positions 2α, 1β, and 16β, followed by conjugation. Most of the metabolites that circulate in the blood are sulfates of 3α, 5β-tetrahydro-levonorgestrel, while excretion occurs predominantly in the form of glucuronides. Some of the parent levonorgestrel also circulates as 17β-sulfate. Metabolic clearance rates may differ among individuals by several-fold, and this may account in part for the wide variation observed in levonorgestrel concentrations among users.

Ethinyl estradiol: Cytochrome P450 enzymes (CYP3A4) in the liver are responsible for the 2-hydroxylation that is the major oxidative reaction. The 2-hydroxy metabolite is further transformed by methylation and glucuronidation prior to urinary and fecal excretion. Levels of Cytochrome P450 (CYP3A) vary widely among individuals and can explain the variation in rates of ethinyl estradiol 2-hydroxylation. Ethinyl estradiol is excreted in the urine and feces as glucuronide and sulfate conjugates, and undergoes enterohepatic circulation.

Excretion

The elimination half-life for levonorgestrel is approximately 36 ± 13 hours at steady state. Levonorgestrel and its metabolites are primarily excreted in the urine (40% to 68%) and about 16% to 48% are excreted in feces. The elimination half-life of ethinyl estradiol is 18 ± 4.7 hours at steady state.

SPECIAL POPULATIONS

Race

Based on the pharmacokinetic study with levonorgestrel and ethinyl estradiol, there are no apparent differences in pharmacokinetic parameters among women of different races.

Hepatic Insufficiency

No formal studies have evaluated the effect of hepatic disease on the disposition of levonorgestrel and ethinyl estradiol. However, steroid hormones may be poorly metabolized in patients with impaired liver function.

Renal Insufficiency

No formal studies have evaluated the effect of renal disease on the disposition of levonorgestrel and ethinyl estradiol.

Drug-Drug Interactions

See PRECAUTIONS Section-DRUG INTERACTIONS

INDICATIONS AND USAGE

Levonorgestrel and ethinyl estradiol tablets USP, 0.1 mg and 0.02 mg are indicated for the prevention of pregnancy in women who elect to use oral contraceptives as a method of contraception.

Oral contraceptives are highly effective. Table II lists the typical accidental pregnancy rates for users of combination oral contraceptives and other methods of contraception. The efficacy of these contraceptive methods, except sterilization, the IUD, and Norplant® System, depends upon the reliability with which they are used. Correct and consistent use of methods can result in lower failure rates.

Table II: Percentage of Women Experiencing an Unintended Pregnancy During the First Year of Typical Use and the First Year of Perfect Use of Contraception and the Percentage Continuing Use at the End of the First Year. United States.
 | Header$% of Women Experiencing an |  | % of Women Continuing
 | Unintended Pregnancy within the |  | Use at One Year [Among couples attempting to avoid pregnancy, the percentage who continue to use a method for one year.]
 | First Year of Use
Method | Typical Use [Among typical couples who initiate use of a method (not necessarily for the first time), the percentage who experience an accidental pregnancy during the first year if they do not stop use for any other reason.] | Perfect Use [Among couples who initiate use of a method (not necessarily for the first time) and who use it perfectly (both consistently and correctly), the percentage who experience an accidental pregnancy during the first year if they do not stop use for any other reason.]
(1) | (2) | (3) | (4)
Chance [The percents becoming pregnant in columns (2) and (3) are based on data from populations where contraception is not used and from women who cease using contraception in order to become pregnant. Among such populations, about 89% become pregnant within one year. This estimate was lowered slightly (to 85%) to represent the percent who would become pregnant within one year among women now relying on reversible methods of contraception if they abandoned contraception altogether.] | 85 | 85
Spermicides [Foams, creams, gels, vaginal suppositories, and vaginal film.] | 26 | 6 | 40
Periodic abstinence | 25 |  | 63
Calendar |  | 9
Ovulation Method |  | 3
Sympto-Thermal [Cervical mucus (ovulation) method supplemented by calendar in the pre-ovulatory and basal body temperature in the post-ovulatory phases.] |  | 2
Post-Ovulation |  | 1
Cap [With spermicidal cream or jelly.]
Parous Women | 40 | 26 | 42
Nulliparous Women | 20 | 9 | 56
Sponge
Parous Women | 40 | 20 | 42
Nulliparous Women | 20 | 9 | 56
Diaphragm | 20 | 6 | 56
Withdrawal | 19 | 4
Condom [Without spermicides.]
Female (Reality) | 21 | 5 | 56
Male | 14 | 3 | 61
Pill | 5 |  | 71
Progestin only |  | 0.5
Combined |  | 0.1
IUD
Progesterone T | 2.0 | 1.5 | 81
Copper T380A | 0.8 | 0.6 | 78
LNg 20 | 0.1 | 0.1 | 81
Depo-Provera® | 0.3 | 0.3 | 70
Levonorgestrel Implants (Norplant®) | 0.05 | 0.05 | 88
Female Sterilization | 0.5 | 0.5 | 100
Emergency Contraceptive Pills: The FDA has concluded that certain combined oral contraceptives containing ethinyl estradiol and norgestrel or levonorgestrel are safe and effective for use as postcoital emergency contraception. Treatment initiated within 72 hours after unprotected intercourse reduces the risk of pregnancy by at least 75%.^9
Lactation Amenorrhea Method: LAM is a highly effective, temporary method of contraception.10
Source: Trussell J. Contraceptive efficacy. In: Hatcher RA, Trussell J, Stewart F, Cates W, Stewart GK, Kowel D, Guest F. Contraceptive Technology: Seventeenth Revised Edition. New York NY: Irvington Publishers; 1998.

In a clinical trial with levonorgestrel and ethinyl estradiol tablets, 1,477 subjects had 7,720 cycles of use and a total of 5 pregnancies were reported. This represents an overall pregnancy rate of 0.84 per 100 woman-years. This rate includes patients who did not take the drug correctly. One or more pills were missed during 1,479 (18.8%) of the 7,870 cycles; thus all tablets were taken during 6,391 (81.2%) of the 7,870 cycles. Of the total 7,870 cycles, a total of 150 cycles were excluded from the calculation of the Pearl index due to the use of backup contraception and/or missing 3 or more consecutive pills.

CONTRAINDICATIONS

Levonorgestrel and ethinyl estradiol tablets are contraindicated in females who are known to have or develop the following conditions:

Thrombophlebitis or thromboembolic disorders

A history of deep-vein thrombophlebitis or thromboembolic disorders

Cerebrovascular or coronary artery disease (current or past history)

Valvular heart disease with thrombogenic complications

Thrombogenic rhythm disorders

Hereditary or acquired thrombophilias

Major surgery with prolonged immobilization

Diabetes with vascular involvement

Headaches with focal neurological symptoms

Uncontrolled hypertension

Current diagnosis of, or history of, breast cancer, which may be hormonesensitive

Carcinoma of the endometrium or other known or suspected estrogen-dependent neoplasia

Undiagnosed abnormal genital bleeding

Cholestatic jaundice of pregnancy or jaundice with prior pill use

Hepatic adenomas or carcinomas, or active liver disease Known or suspected pregnancy

Hypersensitivity to any of the components of levonorgestrel and ethinyl estradiol tablets.

Are receiving Hepatitis C drug combinations containing ombitasvir/paritaprevir/ritonavir, with or without dasabuvir, due to the potential for ALT elevations (see WARNINGS, RISK OF LIVER ENZYME ELEVATIONS WITH CONCOMITANT HEPATITIS C TREATMENT).

WARNINGS

BOXED WARNING

Cigarette smoking increases the risk of serious cardiovascular side effects from oral-contraceptive use. This risk increases with age and with heavy smoking (15 or more cigarettes per day) and is quite marked in women over 35 years of age. Women who use oral contraceptives should be strongly advised not to smoke.

The use of oral contraceptives is associated with increased risks of several serious conditions including venous and arterial thrombotic and thromboembolic events (such as myocardial infarction, thromboembolism, and stroke), hepatic neoplasia, gallbladder disease, and hypertension, although the risk of serious morbidity or mortality is very small in healthy women without underlying risk factors. The risk of morbidity and mortality increases significantly in the presence of other underlying risk factors such as certain inherited or acquired thrombophilias, hypertension, hyperlipidemias, obesity, diabetes, and surgery or trauma with increased risk of thrombosis (see CONTRAINDICATIONS).

Practitioners prescribing oral contraceptives should be familiar with the following information relating to these risks.

The information contained in this package insert is principally based on studies carried out in patients who used oral contraceptives with higher doses of estrogens and progestogens than those in common use today. The effect of long-term use of the oral contraceptives with lower doses of both estrogens and progestogens remains to be determined.

Throughout this labeling, epidemiological studies reported are of two types: retrospective or case control studies and prospective or cohort studies. Case control studies provide a measure of the relative risk of disease, namely, a ratio of the incidence of a disease among oral-contraceptive users to that among nonusers. The relative risk does not provide information on the actual clinical occurrence of a disease. Cohort studies provide a measure of attributable risk, which is the difference in the incidence of disease between oral-contraceptive users and nonusers. The attributable risk does provide information about the actual occurrence of a disease in the population. For further information, the reader is referred to a text on epidemiological methods.

1. Thromboembolic Disorders and Other Vascular Problems

a. Myocardial Infarction

An increased risk of myocardial infarction has been attributed to oral-contraceptive use. This risk is primarily in smokers or women with other underlying risk factors for coronary-artery disease such as hypertension, hypercholesterolemia, morbid obesity, and diabetes. The relative risk of heart attack for current oral-contraceptive users has been estimated to be two to six. The risk is very low under the age of 30.

Smoking in combination with oral-contraceptive use has been shown to contribute substantially to the incidence of myocardial infarction in women in their mid-thirties or older with smoking accounting for the majority of excess cases. Mortality rates associated with circulatory disease have been shown to increase substantially in smokers over the age of 35 and nonsmokers over the age of 40 (FIGURE II) among women who use oral contraceptives.

CIRCULATORY DISEASE MORTALITY RATES PER 100,000 WOMAN YEARS BY AGE, SMOKING STATUS AND ORAL-CONTRACEPTIVE USE

TABLE II. (Adapted from P.M. Layde and V. Beral, Lancet, 1:541-546, 1981.)

Oral contraceptives may compound the effects of well-known risk factors, such as hypertension, diabetes, hyperlipidemias, age, and obesity. In particular, some progestogens are known to decrease HDL cholesterol and cause glucose intolerance, while estrogens may create a state of hyperinsulinism. Oral contraceptives have been shown to increase blood pressure among users (see section 10 in WARNINGS). Similar effects on risk factors have been associated with an increased risk of heart disease. Oral contraceptives must be used with caution in women with cardiovascular disease risk factors.

b. Venous Thrombosis and Thromboembolism

An increased risk of venous thromboembolic and thrombotic disease associated with the use of oral contraceptives is well established. Case control studies have found the relative risk of users compared to non-users to be 3 for the first episode of superficial venous thrombosis, 4 to 11 for deep-vein thrombosis or pulmonary embolism, and 1.5 to 6 for women with predisposing conditions for venous thromboembolic disease. Cohort studies have shown the relative risk to be somewhat lower, about 3 for new cases and about 4.5 for new cases requiring hospitalization. The approximate incidence of deep-vein thrombosis and pulmonary embolism in users of low dose (<50 mcg ethinyl estradiol) combination oral contraceptives is up to 4 per 10,000 woman-years compared to 0.5-3 per 10,000 woman-years for non-users. However, the incidence is less than that associated with pregnancy (6 per 10,000 woman-years). The excess risk is highest during the first year a woman ever uses a combined oral contraceptive. Venous thromboembolism may be fatal. The risk of thromboembolic disease due to oral contraceptives is not related to length of use and gradually disappears after pill use is stopped.

A two- to four-fold increase in relative risk of postoperative thromboembolic complications has been reported with the use of oral contraceptives. The relative risk of venous thrombosis in women who have predisposing conditions is twice that of women without such medical conditions. If feasible, oral contraceptives should be discontinued at least four weeks prior to and for two weeks after elective surgery of a type associated with an increase in risk of thromboembolism and during and following prolonged immobilization. Since the immediate postpartum period is also associated with an increased risk of thromboembolism, oral contraceptives should be started no earlier than four weeks after delivery in women who elect not to breast-feed or after a midtrimester pregnancy termination.

c. Cerebrovascular Diseases

Oral contraceptives have been shown to increase both the relative and attributable risks of cerebrovascular events (thrombotic and hemorrhagic strokes), although, in general, the risk is greatest among older (>35 years), hypertensive women who also smoke. Hypertension was found to be a risk factor for both users and nonusers, for both types of strokes, while smoking interacted to increase the risk for hemorrhagic strokes.

In a large study, the relative risk of thrombotic strokes has been shown to range from 3 for normotensive users to 14 for users with severe hypertension. The relative risk of hemorrhagic stroke is reported to be 1.2 for nonsmokers who used oral contraceptives, 2.6 for smokers who did not use oral contraceptives, 7.6 for smokers who used oral contraceptives, 1.8 for normotensive users and 25.7 for users with severe hypertension. The attributable risk is also greater in older women. Oral contraceptives also increase the risk for stroke in women with other underlying risk factors such as certain inherited or acquired thrombophilias. Women with migraine (particularly migraine/headaches with focal neurological symptoms, see CONTRAINDICATIONS) who take combination oral contraceptives may be at an increased risk of stroke.

d. Dose-Related Risk of Vascular Disease From Oral Contraceptives

A positive association has been observed between the amount of estrogen and progestogen in oral contraceptives and the risk of vascular disease. A decline in serum high-density lipoproteins (HDL) has been reported with many progestational agents. A decline in serum high-density lipoproteins has been associated with an increased incidence of ischemic heart disease. Because estrogens increase HDL cholesterol, the net effect of an oral contraceptive depends on a balance achieved between doses of estrogen and progestogen and the nature and absolute amount of progestogen used in the contraceptive. The amount of both hormones should be considered in the choice of an oral contraceptive.

Minimizing exposure to estrogen and progestogen is in keeping with good principles of therapeutics. For any particular estrogen/progestogen combination, the dosage regimen prescribed should be one which contains the least amount of estrogen and progestogen that is compatible with a low failure rate and the needs of the individual patient. New acceptors of oral-contraceptive agents should be started on preparations containing the lowest estrogen content which is judged appropriate for the individual patient.

e. Persistence of Risk of Vascular Disease

There are two studies which have shown persistence of risk of vascular disease for ever-users of oral contraceptives. In a study in the United States, the risk of developing myocardial infarction after discontinuing oral contraceptives persists for at least 9 years for women 40-49 years who had used oral contraceptives for five or more years, but this increased risk was not demonstrated in other age groups.

In another study in Great Britain, the risk of developing cerebrovascular disease persisted for at least 6 years after discontinuation of oral contraceptives, although excess risk was very small. However, both studies were performed with oral contraceptive formulations containing 50 mcg or higher of estrogens.

2. Estimates of Mortality From Contraceptive Use

One study gathered data from a variety of sources which have estimated the mortality rate associated with different methods of contraception at different ages (TABLE III). These estimates include the combined risk of death associated with contraceptive methods plus the risk attributable to pregnancy in the event of method failure. Each method of contraception has its specific benefits and risks. The study concluded that with the exception of oral-contraceptive users 35 and older who smoke and 40 and older who do not smoke, mortality associated with all methods of birth control is less than that associated with childbirth. The observation of a possible increase in risk of mortality with age for oral-contraceptive users is based on data gathered in the 1970's- but not reported until 1983. However, current clinical practice involves the use of lower estrogen dose formulations combined with careful restriction of oral-contraceptive use to women who do not have the various risk factors listed in this labeling.

Because of these changes in practice and, also, because of some limited new data which suggest that the risk of cardiovascular disease with the use of oral contraceptives may now be less than previously observed, the Fertility and Maternal Health Drugs Advisory Committee was asked to review the topic in 1989. The Committee concluded that although cardiovascular disease risks may be increased with oral-contraceptive use after age 40 in healthy nonsmoking women (even with the newer low-dose formulations), there are greater potential health risks associated with pregnancy in older women and with the alternative surgical and medical procedures which may be necessary if such women do not have access to effective and acceptable means of contraception.

Therefore, the Committee recommended that the benefits of oral-contraceptive use by healthy nonsmoking women over 40 may outweigh the possible risks. Of course, older women, as all women who take oral contraceptives, should take the lowest possible dose formulation that is effective.

TABLE III: ANNUAL NUMBER OF BIRTH-RELATED OR METHOD-RELATED DEATHS ASSOCIATED WITH CONTROL OF FERTILITY PER 100,000 NONSTERILE WOMEN, BY FERTILITY-CONTROL METHOD AND ACCORDING TO AGE
Header$ Method of control and outcome | 15–19 | 20–24 | 25–29 | 30–34 | 35–39 | 40–44
No fertility-control methods [Deaths are birth related] | 7.0 | 7.4 | 9.1 | 14.8 | 25.7 | 28.2
Oral contraceptives
nonsmoker [Deaths are method related] | 0.3 | 0.5 | 0.9 | 1.9 | 13.8 | 31.6
Oral contraceptives
smoker | 2.2 | 3.4 | 6.6 | 13.5 | 51.1 | 117.2
IUD | 0.8 | 0.8 | 1.0 | 1.0 | 1.4 | 1.4
Condom | 1.1 | 1.6 | 0.7 | 0.2 | 0.3 | 0.4
Diaphragm/spermicide | 1.9 | 1.2 | 1.2 | 1.3 | 2.2 | 2.8
Periodic abstinence | 2.5 | 1.6 | 1.6 | 1.7 | 2.9 | 3.6
Adapted from H.W. Ory, Family Planning Perspectives, 15: 57-63, 1983.

3. Malignant Neoplasms

Breast Cancer

Levonorgestrel and ethinyl estradiol tablets is contraindicated in females who currently have or have had breast cancer because breast cancer may be hormonally sensitive [see CONTRAINDICATIONS]. Epidemiology studies have not found a consistent association between use of combined oral contraceptives (COCs) and breast cancer risk. Studies do not show an association between ever (current or past) use of COCs and risk of breast cancer. However, some studies report a small increase in the risk of breast cancer among current or recent users (<6 months since last use) and current users with longer duration of COC use [see POSTMARKETING EXPERIENCE].

Cervical Cancer

Some studies suggest that oral contraceptive use has been associated with an increase in the risk of cervical intraepithelial neoplasia or invasive cervical cancer in some populations of women. However, there continues to be controversy about the extent to which such findings may be due to differences in sexual behavior and other factors.

In spite of many studies of the relationship between combination oral contraceptive use and breast and cervical cancers, a cause-and-effect relationship has not been established.

4. Hepatic Neoplasia

Benign hepatic adenomas are associated with oral-contraceptive use, although the incidence of these benign tumors is rare in the United States. Indirect calculations have estimated the attributable risk to be in the range of 3.3 cases/100,000 for users, a risk that increases after four or more years of use. Rupture of rare, benign, hepatic adenomas may cause death through intra-abdominal hemorrhage.

Studies from Britain have shown an increased risk of developing hepatocellular carcinoma in long-term (>8 years) oral-contraceptive users. However, these cancers are extremely rare in the U.S. and the attributable risk (the excess incidence) of liver cancers in oral-contraceptive users approaches less than one per million users.

5. Risk Of Liver Enzyme Elevations With Concomitant Hepatitis C Treatment

During clinical trials with the Hepatitis C combination drug regimen that contains ombitasvir/paritaprevir/ritonavir, with or without dasabuvir, ALT elevations greater than 5 times the upper limit of normal (ULN), including some cases greater than 20 times the ULN, were significantly more frequent in women using ethinyl estradiol-containing medications such as COCs. Discontinue levonorgestrel and ethinyl estradiol tablets prior to starting therapy with the combination drug regimen ombitasvir/paritaprevir/ritonavir, with or without dasabuvir [see CONTRAINDICATIONS]. Levonorgestrel and ethinyl estradiol tablets can be restarted approximately 2 weeks following completion of treatment with the combination drug regimen.

6. Ocular Lesions

There have been clinical case reports of retinal thrombosis associated with the use of oral contraceptives that may lead to partial or complete loss of vision. Oral contraceptives should be discontinued if there is unexplained partial or complete loss of vision; onset of proptosis or diplopia; papilledema; or retinal vascular lesions. Appropriate diagnostic and therapeutic measures should be undertaken immediately.

7. Oral-Contraceptive Use Before Or During Early Pregnancy

Extensive epidemiological studies have revealed no increased risk of birth defects in infants born to women who have used oral contraceptives prior to pregnancy. Studies also do not suggest a teratogenic effect, particularly insofar as cardiac anomalies and limb-reduction defects are concerned, when taken inadvertently during early pregnancy (see CONTRAINDICATIONS section).

The administration of oral contraceptives to induce withdrawal bleeding should not be used as a test for pregnancy. Oral contraceptives should not be used during pregnancy to treat threatened or habitual abortion.

It is recommended that for any patient who has missed two consecutive periods, pregnancy should be ruled out. If the patient has not adhered to the prescribed schedule, the possibility of pregnancy should be considered at the time of the first missed period. Oral-contraceptive use should be discontinued if pregnancy is confirmed.

8. Gallbladder Disease

Combination oral contraceptives may worsen existing gallbladder disease and may accelerate the development of this disease in previously asymptomatic women. Earlier studies have reported an increased lifetime relative risk of gallbladder surgery in users of oral contraceptives and estrogens. More recent studies, however, have shown that the relative risk of developing gallbladder disease among oral-contraceptive users may be minimal. The recent findings of minimal risk may be related to the use of oral-contraceptive formulations containing lower hormonal doses of estrogens and progestogens.

9. Carbohydrate And Lipid Metabolic Effects

Oral contraceptives have been shown to cause glucose intolerance in a significant percentage of users. Oral contraceptives containing greater than 75 mcg of estrogens cause hyperinsulinism, while lower doses of estrogen cause less glucose intolerance. Progestogens increase insulin secretion and create insulin resistance, this effect varying with different progestational agents. However, in the nondiabetic woman, oral contraceptives appear to have no effect on fasting blood glucose. Because of these demonstrated effects, prediabetic and diabetic women should be carefully observed while taking oral contraceptives.

A small proportion of women will have persistent hypertriglyceridemia while on the pill. As discussed earlier (see WARNINGS, 1a. and 1d.; PRECAUTIONS, 3.), changes in serum triglycerides and lipoprotein levels have been reported in oral-contraceptive users.

10. Elevated Blood Pressure

An increase in blood pressure has been reported in women taking oral contraceptives and this increase is more likely in older oral-contraceptive users and with continued use. Data from the Royal College of General Practitioners and subsequent randomized trials have shown that the incidence of hypertension increases with increasing quantities of progestogens.

Women with a history of hypertension or hypertension-related diseases, or renal disease should be encouraged to use another method of contraception. If women with hypertension elect to use oral contraceptives, they should be monitored closely and if significant elevation of blood pressure occurs, oral contraceptives should be discontinued (see CONTRAINDICATIONS section). For most women, elevated blood pressure will return to normal after stopping oral contraceptives, and there is no difference in the occurrence of hypertension among ever- and never-users.

11. Headache

The onset or exacerbation of migraine or development of headache with a new pattern that is recurrent, persistent, or severe requires discontinuation of oral contraceptives and evaluation of the cause. (See WARNINGS, 1c. and CONTRAINDICATIONS.)

12. Bleeding Irregularities

Breakthrough bleeding and spotting are sometimes encountered in patients on oral contraceptives, especially during the first three months of use. The type and dose of progestogen may be important. If bleeding persists or recurs, nonhormonal causes should be considered and adequate diagnostic measures taken to rule out malignancy or pregnancy in the event of breakthrough bleeding, as in the case of any abnormal vaginal bleeding. If pathology has been excluded, time or a change to another formulation may solve the problem. In the event of amenorrhea, pregnancy should be ruled out.

Some women may encounter post-pill amenorrhea or oligomenorrhea (possibly with anovulation), especially when such a condition was preexistent.

13. Ectopic Pregnancy

Ectopic as well as intrauterine pregnancy may occur in contraceptive failures.

PRECAUTIONS

1. General

Patients should be counseled that oral contraceptives do not protect against transmission of HIV (AIDS) and other sexually transmitted diseases (STDs) such as chlamydia, genital herpes, genital warts, gonorrhea, hepatitis B, and syphilis.

2. Physical Examination And Follow-Up

A periodic personal and family medical history and complete physical examination are appropriate for all women, including women using oral contraceptives. The physical examination, however, may be deferred until after initiation of oral contraceptives if requested by the woman and judged appropriate by the clinician. The physical examination should include special reference to blood pressure, breasts, abdomen, and pelvic organs, including cervical cytology, and relevant laboratory tests. In case of undiagnosed, persistent, or recurrent abnormal vaginal bleeding, appropriate diagnostic measures should be conducted to rule out malignancy. Women with a strong family history of breast cancer or who have breast nodules should be monitored with particular care.

3. Lipid Disorders

Women who are being treated for hyperlipidemias should be followed closely if they elect to use oral contraceptives. Some progestogens may elevate LDL levels and may render the control of hyperlipidemias more difficult. (See WARNINGS, 1a., 1d., and 8.)

A small proportion of women will have adverse lipid changes while taking oral contraceptives. Nonhormonal contraception should be considered in women with uncontrolled dyslipidemias. Persistent hypertriglyceridemia may occur in a small population of combination oral contraceptive users. Elevations of plasma triglycerides may lead to pancreatitis and other complications.

4. Liver Function

If jaundice develops in any woman receiving such drugs, the medication should be discontinued. Steroid hormones may be poorly metabolized in patients with impaired liver function.

5. Fluid Retention

Oral contraceptives may cause some degree of fluid retention. They should be prescribed with caution, and only with careful monitoring, in patients with conditions which might be aggravated by fluid retention.

6. Emotional Disorders

Patients becoming significantly depressed while taking oral contraceptives should stop the medication and use an alternate method of contraception in an attempt to determine whether the symptom is drug related. Women with a history of depression should be carefully observed and the drug discontinued if depression recurs to a serious degree.

7. Contact Lenses

Contact-lens wearers who develop visual changes or changes in lens tolerance should be assessed by an ophthalmologist.

8. Gastrointestinal

Diarrhea and/or vomiting may reduce hormone absorption resulting in decreased serum concentrations.

9. Drug Interactions

Changes in Contraceptive Effectiveness Associated With Coadministration Of Other Products:

Contraceptive effectiveness may be reduced when hormonal contraceptives are coadministered with antibiotics, anticonvulsants, and other drugs that increase the metabolism of contraceptive steroids. This could result in unintended pregnancy or breakthrough bleeding. Examples include rifampin, rifabutin, barbiturates, primidone, phenylbutazone, phenytoin, dexamethasone, carbamazepine, felbamate, oxcarbazepine, topiramate, griseofulvin, and modafinil. In such cases a back-up nonhormonal method of birth control should be considered.

Several cases of contraceptive failure and breakthrough bleeding have been reported in the literature with concomitant administration of antibiotics such as ampicillin and other penicillins, and tetracyclines. However, clinical pharmacology studies investigating drug interactions between combined oral contraceptives and these antibiotics have reported inconsistent results.

Several of the anti-HIV protease inhibitors have been studied with co-administration of oral combination hormonal contraceptives; significant changes (increase and decrease) in the plasma levels of the estrogen and progestin have been noted in some cases. The safety and efficacy of oral contraceptive products may be affected with coadministration of anti-HIV protease inhibitors. Healthcare providers should refer to the label of the individual anti-HIV protease inhibitors for further drug-drug interaction information.

Herbal products containing St. John's Wort (Hypericum perforatum) may induce hepatic enzymes (cytochrome P450) and p-glycoprotein transporter and may reduce the effectiveness of contraceptive steroids. This may also result in breakthrough bleeding.

Concomitant Use with HCV Combination Therapy – Liver Enzyme Elevation

Do not co-administer levonorgestrel and ethinyl estradiol tablets with HCV drug combinations containing ombitasvir/paritaprevir/ritonavir, with or without dasabuvir, due to potential for ALT elevations (see WARNINGS, RISK OF LIVER ENZYME ELEVATIONS WITH CONCOMITANT HEPATITIS C TREATMENT).

Increase In Plasma Levels Associated With Co-Administered Drugs:

Co-administration of atorvastatin and certain oral contraceptives containing ethinyl estradiol increases AUC values for ethinyl estradiol by approximately 20%. Ascorbic acid and acetaminophen increase the bioavailability of ethinyl estradiol since these drugs act as competitive inhibitors for sulfation of ethinyl estradiol in the gastrointestinal wall, a known pathway of elimination for ethinyl estradiol. CYP 3A4 inhibitors such as indinavir, itraconazole, ketoconazole, fluconazole, and troleandomycin may increase plasma hormone levels. Troleandomycin may also increase the risk of intrahepatic cholestasis during coadministration with combination oral contraceptives.

Changes in Plasma Levels of Co-Administered Drugs:

Combination hormonal contraceptives containing some synthetic estrogens (eg, ethinyl estradiol) may inhibit the metabolism of other compounds. Increased plasma concentrations of cyclosporin, prednisolone and other corticosteroids, and theophylline have been reported with concomitant administration of oral contraceptives. Decreased plasma concentrations of acetaminophen and increased clearance of temazepam, salicylic acid, morphine, and clofibric acid, due to induction of conjugation (particularly glucuronidation), have been noted when these drugs were administered with oral contraceptives.

The prescribing information of concomitant medications should be consulted to identify potential interactions.

10. Interactions With Laboratory Tests

Certain endocrine- and liver-function tests and blood components may be affected by oral contraceptives:

a. Increased prothrombin and factors VII, VIII, IX, and X; decreased antithrombin 3; increased norepinephrine-induced platelet aggregability.

b. Increased thyroid-binding globulin (TBG) leading to increased circulating total thyroid hormone, as measured by protein-bound iodine (PBI), T4 by column or by radioimmunoassay. Free T3 resin uptake is decreased, reflecting the elevated TBG; free T4 concentration is unaltered.

c. Other binding proteins may be elevated in serum i.e., corticosteroid binding globulin (CBG), sex hormone-binding globulins (SHBG) leading to increased levels of total circulating corticosteroids and sex steroids respectively. Free or biologically active hormone concentrations are unchanged.

d. Triglycerides may be increased and levels of various other lipids and lipoproteins may be affected.

e. Glucose tolerance may be decreased.

f. Serum folate levels may be depressed by oral-contraceptive therapy. This may be of clinical significance if a woman becomes pregnant shortly after discontinuing oral contraceptives.

11. Carcinogenesis

See WARNINGS section.

12. Pregnancy

See CONTRAINDICATIONS and WARNINGS sections.

13. Nursing Mothers

Small amounts of oral-contraceptive steroids and/or metabolites have been identified in the milk of nursing mothers, and a few adverse effects on the child have been reported, including jaundice and breast enlargement. In addition, combination oral contraceptives given in the postpartum period may interfere with lactation by decreasing the quantity and quality of breast milk. If possible, the nursing mother should be advised not to use combination oral contraceptives but to use other forms of contraception until she has completely weaned her child.

14. Pediatric Use

Safety and efficacy of levonorgestrel and ethinyl estradiol tablets have been established in women of reproductive age. Safety and efficacy are expected to be the same for postpuberal adolescents under the age of 16 and for users 16 years and older. Use of levonorgestrel and ethinyl estradiol tablets before menarche is not indicated.

15. Geriatric Use

Levonorgestrel and ethinyl estradiol tablet has not been studied in women over 65 years of age and is not indicated in this population.

16. Information For The Patient

See Patient Labeling Printed Below.

ADVERSE REACTIONS

Post Marketing Experience

Five studies that compared breast cancer risk between ever-users (current or past use) of COCs and never-users of COCs reported no association between ever use of COCs and breast cancer risk, with effect estimates ranging from 0.90 - 1.12 (Figure 1).

Three studies compared breast cancer risk between current or recent COC users (<6 months since last use) and never users of COCs (Figure 1). One of these studies reported no association between breast cancer risk and COC use. The other two studies found an increased relative risk of 1.19 - 1.33 with current or recent use. Both of these studies found an increased risk of breast cancer with current use of longer duration, with relative risks ranging from 1.03 with less than one year of COC use to approximately 1.4 with more than 8-10 years of COC use.

Figure 1: Risk of Breast Cancer with Combined Oral Contraceptive Use

RR = relative risk; OR = odds ratio; HR = hazard ratio. "ever COC" are females with current or past COC use; "never COC use" are females that never used COCs.

An increased risk of the following serious adverse reactions (see WARNINGSsection for additional information) has been associated with the use of oral contraceptives:

Thromboembolic and thrombotic disorders and other vascular problems (including thrombophlebitis and venous thrombosis with or without pulmonary embolism, mesenteric thrombosis, arterial thromboembolism, myocardial infarction, cerebral hemorrhage, cerebral thrombosis), carcinoma of the reproductive organs and breasts, hepatic neoplasia (including hepatic adenomas or benign liver tumors), ocular lesions (including retinal vascular thrombosis), gallbladder disease, carbohydrate and lipid effects, elevated blood pressure, and headache including migraine.

The following adverse reactions have been reported in patients receiving oral contraceptives and are believed to be drug related (alphabetically listed):

Acne

Amenorrhea

Anaphylactic/anaphylactoid reactions, including urticaria, angioedema, and severe reactions with respiratory and circulatory symptoms

Breast changes: tenderness, pain, enlargement, secretion

Budd-Chiari syndrome

Cervical erosion and secretion, change in

Cholestatic jaundice

Chorea, exacerbation of

Colitis

Contact lenses, intolerance to

Corneal curvature (steepening), change in

Dizziness

Edema/fluid retention

Erythema multiforme

Erythema nodosum

Gastrointestinal symptoms (such as abdominal pain, cramps, and bloating) Hirsutism

Infertility after discontinuation of treatment, temporary

Lactation, diminution in, when given immediately postpartum

Libido, change in

Melasma/chloasma which may persist Menstrual flow, change in

Mood changes, including depression

Nausea

Nervousness

Pancreatitis

Porphyria, exacerbation of

Rash (allergic)

Scalp hair, loss of

Serum folate levels, decrease in

Spotting

Systemic lupus erythematosus, exacerbation of

Unscheduled bleeding

Vaginitis, including candidiasis

Varicose veins, aggravation of

Vomiting Weight or appetite (increase or decrease), change in

The following adverse reactions have been reported in users of oral contraceptives:

Cataracts

Cystitis-like syndrome

Dysmenorrhea

Hemolytic uremic syndrome

Hemorrhagic eruption

Optic neuritis, which may lead to partial or complete loss of vision

Premenstrual syndrome

Renal function, impaired

OVERDOSAGE

Symptoms of oral contraceptive overdosage in adults and children may include nausea, vomiting, and drowsiness/fatigue; withdrawal bleeding may occur in females. There is no specific antidote and further treatment of overdose, if necessary, is directed to the symptoms.

Noncontraceptive Health Benefits

The following noncontraceptive health benefits related to the use of oral contraceptives are supported by epidemiological studies which largely utilized oral-contraceptive formulations containing doses exceeding 0.035 mg of ethinyl estradiol or 0.05 mg of mestranol.

Effects on menses:

Increased menstrual cycle regularity

Decreased blood loss and decreased incidence of iron-deficiency anemia

Decreased incidence of dysmenorrhea

Effects related to inhibition of ovulation:

Decreased incidence of functional ovarian cysts

Decreased incidence of ectopic pregnancies

Effects from long-term use:

Decreased incidence of fibroadenomas and fibrocystic disease of the breast Decreased incidence of acute pelvic inflammatory disease

Decreased incidence of endometrial cancer

Decreased incidence of ovarian cancer

DOSAGE AND ADMINISTRATION

To achieve maximum contraceptive effectiveness, levonorgestrel and ethinyl estradiol tablets must be taken exactly as directed and at intervals not exceeding 24 hours.

The dosage of levonorgestrel and ethinyl estradiol tablets is one white tablet daily for 21 consecutive days, followed by one orange inert tablet daily for 7 consecutive days, according to the prescribed schedule.

It is recommended that levonorgestrel and ethinyl estradiol tablets be taken at the same time each day.

During The First Cycle Of Use

The possibility of ovulation and conception prior to initiation of medication should be considered. The patient should be instructed to begin taking levonorgestrel and ethinyl estradiol tablets on either the first Sunday after the onset of menstruation (Sunday Start) or on Day 1 of menstruation (Day 1 Start).

Sunday start:

The patient is instructed to begin taking levonorgestrel and ethinyl estradiol tablets on the first Sunday after the onset of menstruation. If menstruation begins on a Sunday, the first tablet (white) is taken that day. One white tablet should be taken daily for 21 consecutive days, followed by one orange inert tablet daily for seven consecutive days. Withdrawal bleeding should usually occur within three days following discontinuation of white tablets and may not have finished before the next pack is started. During the first cycle, contraceptive reliance should not be placed on levonorgestrel and ethinyl estradiol tablets until a white tablet has been taken daily for 7 consecutive days, and a nonhormonal back-up method of birth control should be used during those 7 days.

Day 1 start:

During the first cycle of medication, the patient is instructed to begin taking levonorgestrel and ethinyl estradiol tablets during the first 24 hours of her period (day one of her menstrual cycle). One white tablet should be taken daily for 21 consecutive days, followed by one orange inert tablet daily for seven consecutive days. Withdrawal bleeding should usually occur within three days following discontinuation of white tablets may not have finished before the next pack is started. If medication is begun on day one of the menstrual cycle, no back-up contraception is necessary. If levonorgestrel and ethinyl estradiol tablets are started later than day one of the first menstrual cycle or postpartum, contraceptive reliance should not be placed on levonorgestrel and ethinyl estradiol tablets until after the first 7 consecutive days of administration, and a nonhormonal back-up method of birth control should be used during those 7 days.

After the first cycle of use

The patient begins her next and all subsequent courses of tablets on the day after taking her last orange tablet. She should follow the same dosing schedule: 21 days on white tablets followed by 7 days on orange tablets. If in any cycle the patient starts tablets later than the proper day, she should protect herself against pregnancy by using a nonhormonal back-up method of birth control until she has taken a white tablet daily for 7 consecutive days.

Switching from another hormonal method of contraception

When the patient is switching from a 21-day regimen of tablets, she should wait 7 days after her last tablet before she starts levonorgestrel and ethinyl estradiol tablets. She will probably experience withdrawal bleeding during that week. She should be sure that no more than 7 days pass after her previous 21-day regimen. When the patient is switching from a 28-day regimen of tablets, she should start her first pack of levonorgestrel and ethinyl estradiol tablets on the day after her last tablet. She should not wait any days between packs. The patient may switch any day from a progestin-only pill and should begin levonorgestrel and ethinyl estradiol tablets the next day. If switching from an implant or injection, the patient should start levonorgestrel and ethinyl estradiol tablets on the day of implant removal or, if using an injection, the day the next injection would be due. In switching from a progestin-only pill, injection, or implant, the patient should be advised to use a nonhormonal back-up method of birth control for the first 7 days of tablet-taking.

If spotting or breakthrough bleeding occurs

If spotting or breakthrough bleeding occur, the patient is instructed to continue on the same regimen. This type of bleeding is usually transient and without significance; however, if the bleeding is persistent or prolonged, the patient is advised to consult her physician.

Risk of pregnancy if tablets are missed

While there is little likelihood of ovulation occurring if only one or two white tablets are missed, the possibility of ovulation increases with each successive day that scheduled white tablets are missed. Although the occurrence of pregnancy is unlikely if levonorgestrel and ethinyl estradiol tablets are taken according to directions, if withdrawal bleeding does not occur, the possibility of pregnancy must be considered. If the patient has not adhered to the prescribed schedule (missed one or more tablets or started taking them on a day later than she should have), the probability of pregnancy should be considered at the time of the first missed period and appropriate diagnostic measures taken. If the patient has adhered to the prescribed regimen and misses two consecutive periods, pregnancy should be ruled out.

The risk of pregnancy increases with each active (white) tablet missed. For additional patient instructions regarding missed tablets, see the WHAT TO DO IF YOU MISS PILLS section in the DETAILED PATIENT LABELING below.

Use after pregnancy, abortion or miscarriage

Levonorgestrel and ethinyl estradiol tablets may be initiated no earlier than day 28 postpartum in the nonlactating mother or after a second trimester abortion due to the increased risk for thromboembolism (see CONTRAINDICATIONS, WARNINGS, and PRECAUTIONSconcerning thromboembolic disease). The patient should be advised to use a non-hormonal back-up method for the first 7 days of tablet taking.

Levonorgestrel and ethinyl estradiol tablets may be initiated immediately after a first trimester abortion or miscarriage. If the patient starts levonorgestrel and ethinyl estradiol tablets immediately, back-up contraception is not needed.

HOW SUPPLIED

Levonorgestrel and ethinyl estradiol tablets USP, 0.1 mg/0.02 mg are available in 3 blisters, each containing 28 tablets as follows.

Each blister contains 21 white to off white round bevel edged tablets each containing 0.1 mg levonorgestrel and 0.02 mg ethinyl estradiol, debossed with "LU" on one side and "T21" on the other side and 7 orange round bevel edged inert tablets debossed with "LU" on one side and "T22" on the other side.

They are supplied as follows:

Levonorgestrel and ethinyl estradiol tablets USP, 0.1 mg/0.02 mg are available in a blister (NDC 68180-854-71) of 28 tablets, such 3 blisters are packed in a carton (NDC 68180-854-73).

Store at 25° C (77° F); excursions permitted to 15°- 30° C (59°- 86° F) [see USP Controlled Room Temperature]

Distributed by:

Lupin Pharmaceuticals, Inc.

Naples, FL 34108

United States

Manufactured by:

Lupin Limited

Pithampur (M.P.) - 454 775

INDIA

Revised: December 2024

BRIEF SUMMARY PATIENT PACKAGE INSERT

Levonorgestrel and Ethinyl Estradiol Tablets USP, 0.1 mg/0.02 mg

Rx only

This product (like all oral contraceptives) is intended to prevent pregnancy. Oral contraceptives do not protect against transmission of HIV (AIDS) and other sexually transmitted diseases (STDs) such as chlamydia, genital herpes, genital warts, gonorrhea, hepatitis B, and syphilis.

Oral contraceptives, also known as "birth-control pills" or "the pill," are taken to prevent pregnancy, and when taken correctly, have a failure rate of approximately 1.0% per year (1 pregnancy per 100 women per year of use) when used without missing any pills. The average failure rate of large numbers of pill users is approximately 5% per year (5 pregnancies per 100 women per year of use) when women who miss pills are included. For most women oral contraceptives are also free of serious or unpleasant side effects. However, forgetting to take pills considerably increases the chances of pregnancy.

For the majority of women, oral contraceptives can be taken safely. But there are some women who are at high risk of developing certain serious diseases that can be life-threatening or may cause temporary or permanent disability or death. The risks associated with taking oral contraceptives increase significantly if you:

- smoke.
- have high blood pressure, diabetes, high cholesterol, or a tendency to form blood clots.
- have or have had clotting disorders, heart attack, stroke, angina pectoris, cancer of the breast or sex organs, jaundice, malignant or benign liver tumors, or major surgery with prolonged immobilization.
- have headaches with neurological symptoms.

You should not take the pill if you suspect you are pregnant or have unexplained vaginal bleeding.

Although cardiovascular disease risks may be increased with oral-contraceptive use after age 40 in healthy, nonsmoking women, there are also greater potential health risks associated with pregnancy in older women.

BOXED WARNING

Cigarette smoking increases the risk of serious adverse effects on the heart and blood vessels from oral-contraceptive use. This risk increases with age and with heavy smoking (15 or more cigarettes per day) and is quite marked in women over 35 years of age. Women who use oral contraceptives should not smoke.

Most side effects of the pill are not serious. The most common such effects are nausea, vomiting, bleeding between menstrual periods, weight gain, breast tenderness, and difficulty wearing contact lenses. These side effects, especially nausea and vomiting, may subside within the first three months of use.

The serious side effects of the pill occur very infrequently, especially if you are in good health and do not smoke. However, you should know that the following medical conditions have been associated with or made worse by the pill:

1. Blood clots in the legs (thrombophlebitis) and lungs (pulmonary embolism), blockage or rupture of a blood vessel in the brain (stroke), blockage of blood vessels in the heart (heart attack and angina pectoris) or other organs of the body. As mentioned above, smoking increases the risk of heart attacks and strokes and subsequent serious medical consequences. Women with migraine also may be at increased risk of stroke with pill use.

2. Liver tumors, which may rupture and cause severe bleeding. A possible but not definite association has been found with the pill and liver cancer. However, liver cancers are extremely rare. The chance of developing liver cancer from using the pill is thus even rarer.

3. High blood pressure, although blood pressure usually returns to normal when the pill is stopped.

The symptoms associated with these serious side effects are discussed in the detailed leaflet given to you with your supply of pills. Notify your health-care provider if you notice any unusual physical disturbances while taking the pill. In addition, drugs such as rifampin, as well as some anticonvulsants and some antibiotics, herbal preparations containing St. John's Wort (Hypericum perforatum), and HIV/AIDS drugs may decrease oral-contraceptive effectiveness.

There may be slight increases in the risk of breast cancer among current users of hormonal birth control pills with longer duration of use of 8 years or more.

Some studies have found an increase in the incidence of cancer of the cervix in women who use oral contraceptives. However, this finding may be related to factors other than the use of oral contraceptives.

Taking the pill provides some important noncontraceptive benefits. These include less painful menstruation, less menstrual blood loss and anemia, fewer pelvic infections, and fewer cancers of the ovary and the lining of the uterus.

Be sure to discuss any medical condition you may have with your health-care provider. Your health-care provider will take a medical and family history before prescribing oral contraceptives and will examine you. The physical examination may be delayed to another time if you request it and the health-care provider believes that it is appropriate to postpone it. You should be reexamined at least once a year while taking oral contraceptives. The detailed patient information leaflet gives you further information which you should read and discuss with your health-care provider.

HOW TO TAKE LEVONORGESTREL AND ETHINYL ESTRADIOL TABLETS

IMPORTANT POINTS TO REMEMBER

BEFORE YOU START TAKING LEVONORGESTREL AND ETHINYL ESTRADIOL TABLETS:

1. BE SURE TO READ THESE DIRECTIONS:

Before you start taking levonorgestrel and ethinyl estradiol tablets.

And

Anytime you are not sure what to do.

2. THE RIGHT WAY TO TAKE THE PILL IS TO TAKE ONE PILL EVERY DAY AT THE SAME TIME.

If you miss pills you could get pregnant. This includes starting the pack late. The more pills you miss, the more likely you are to get pregnant. See "WHAT TO DO IF YOU MISS PILLS" below.

3. MANY WOMEN HAVE SPOTTING OR LIGHT BLEEDING, OR MAY FEEL SICK TO THEIR STOMACH DURING THE FIRST 1-3 PACKS OF PILLS.

If you feel sick to your stomach, do not stop taking levonorgestrel and ethinyl estradiol tablets. The problem will usually go away. If it doesn't go away, check with your health-care provider.

4. MISSING PILLS CAN ALSO CAUSE SPOTTING OR LIGHT BLEEDING, even when you make up these missed pills.

On the days you take 2 pills to make up for missed pills, you could also feel a little sick to your stomach.

5. IF YOU HAVE VOMITING (within 4 hours after you take your pill), you should follow the instructions for WHAT TO DO IF YOU MISS PILLS. IF YOU HAVE DIARRHEA or IF YOU TAKE SOME MEDICINES, including some antibiotics, your pills may not work as well.

Use a back-up nonhormonal method (such as condoms or spermicide) until you check with your health-care provider.

6. IF YOU HAVE TROUBLE REMEMBERING TO TAKE THE PILL, talk to your health-care provider about how to make pill-taking easier or about using another method of birth control.

7. IF YOU HAVE ANY QUESTIONS OR ARE UNSURE ABOUT THE INFORMATION IN THIS LEAFLET, call your health-care provider.

BEFORE YOU START TAKING LEVONORGESTREL AND ETHINYL ESTRADIOL TABLETS

1. DECIDE WHAT TIME OF DAY YOU WANT TO TAKE YOUR PILL. It is important to take it at about the same time every day.

2. LOOK AT YOUR PILL PACK.

The pill pack has 21 "active" white pills (with hormones) to take for 3 weeks, followed by 1 week of reminder orange pills (without hormones).

3. FIND:

1. where on the pack to start taking pills, and

2. in what order to take the pills (follow the arrow).

4. BE SURE YOU HAVE READY AT ALL TIMES:

ANOTHER KIND OF BIRTH CONTROL (such as condoms or spermicide) to use as a back-up in case you miss pills.

AN EXTRA, FULL PILL PACK.

* For use of day labels, see WHEN TO START THE FIRST PACK OF PILLS below.

WHEN TO START THE FIRST PACK OF PILLS

You have a choice of which day to start taking your first pack of pills.

Decide with your health-care provider which is the best day for you. Pick a time of day which will be easy to remember.

DAY 1 START

1. Take the first "active" white pill of the first pack during the first 24 hours of your period.
2. You will not need to use a back-up nonhormonal method of birth control, since you are starting the pill at the beginning of your period.

SUNDAY START

1. Take the first "active" white pill of the first pack on the Sunday after your period starts, even if you are still bleeding. If your period begins on Sunday, start the pack that same day.
2. Use a nonhormonal method of birth control (such as condoms or spermicide) as a back-up method if you have sex anytime from the Sunday you start your first pack until the next Sunday (7 days).

WHAT TO DO DURING THE MONTH

1. Take one pill at the same time every day until the pack is empty.

Do not skip pills even if you are spotting or bleeding between monthly periods or feel sick to your stomach (nausea).

Do not skip pills even if you do not have sex very often.

2. When you finish a pack:

Start the next pack on the day after your last "reminder" pill. Do not wait any days between packs.

IF YOU SWITCH FROM ANOTHER BRAND OF COMBINATION PILLS

If your previous brand had 21 pills: Wait 7 days to start taking levonorgestrel and ethinyl estradiol tablets. You will probably have your period during that week. Be sure that no more than 7 days pass between the 21-day pack and taking the first white levonorgestrel and ethinyl estradiol tablets ("active" with hormone).

If your previous brand had 28 pills: Start taking the first white levonorgestrel and ethinyl estradiol tablets ("active" with hormone) on the day after your last reminder pill. Do not wait any days between packs.

WHAT TO DO IF YOU MISS PILLS

Levonorgestrel and ethinyl estradiol tablets may not be as effective if you miss white "active" pills, and particularly if you miss the first few or the last few white "active" pills in a pack.

If you MISS 1 white "active" pill:

1. Take it as soon as you remember. Take the next pill at your regular time. This means you may take 2 pills in 1 day.
2. You COULD BECOME PREGNANT if you have sex in the 7 days after you restart your pills. You MUST use a nonhormonal birth-control method (such as condoms or spermicide) as a back-up for those 7 days.

If you MISS 2 white "active" pills in a row in WEEK 1 OR WEEK 2 of your pack:

1. Take 2 pills on the day you remember and 2 pills the next day.
2. Then take 1 pill a day until you finish the pack.
3. You COULD BECOME PREGNANT if you have sex in the 7 days after you restart your pills. You MUST use a nonhormonal birth-control method (such as condoms or spermicide) as a back-up for those 7 days.

If you MISS 2 white "active" pills in a row in THE 3rd WEEK:

1. If you are a Day 1 Starter:

THROW OUT the rest of the pill pack and start a new pack that same day.

If you are a Sunday Starter:

Keep taking 1 pill every day until Sunday.

On Sunday, THROW OUT the rest of the pack and start a new pack of pills that same day.

2. You may not have your period this month but this is expected

However, if you miss your period 2 months in a row, call your health-care provider because you might be pregnant.

3. You COULD BECOME PREGNANT if you have sex in the 7 days after you restart your pills. You MUST use a nonhormonal birth-control method (such as condoms or spermicide) as a back-up for those 7 days.

If you MISS 3 OR MORE white "active" pills in a row (during the first 3 weeks):

1. If you are a Day 1 Starter:

THROW OUT the rest of the pill pack and start a new pack that same day.

If you are a Sunday Starter:

Keep taking 1 pill every day until Sunday.

On Sunday, THROW OUT the rest of the pack and start a new pack of pills that same day.

2. You may not have your period this month but this is expected.

However, if you miss your period 2 months in a row, call your health-care provider because you might be pregnant.

3. You COULD BECOME PREGNANT if you have sex in the 7 days after you restart your pills.

You MUST use a nonhormonal birth-control method (such as condoms or spermicide) as a back-up for those 7 days.

If you forget any of the 7 orange "reminder" pills in Week 4:

THROW AWAY the pills you missed.

Keep taking 1 pill each day until the pack is empty.

You do not need a back-up nonhormonal birth-control method if you start your next pack on time.

FINALLY, IF YOU ARE STILL NOT SURE WHAT TO DO ABOUT THE PILLS YOU HAVE MISSED

Use a BACK-UP NONHORMONAL BIRTH-CONTROL METHOD anytime you have sex.

KEEP TAKING ONE PILL EACH DAY until you can reach your health-care provider.

BIRTH CONTROL AFTER STOPPING THE PILL

If you do not wish to become pregnant after stopping the pill, speak to your health-care provider about another method of birth control.

DETAILED PATIENT LABELING

This product (like all oral contraceptives) is intended to prevent pregnancy. Oral contraceptives do not protect against transmission of HIV (AIDS) and other sexually transmitted diseases (STDs) such as chlamydia, genital herpes, genital warts, gonorrhea, hepatitis B, and syphilis.

INTRODUCTION

Any woman who considers using oral contraceptives (the "birth-control pill" or "the pill") should understand the benefits and risks of using this form of birth control. This leaflet will give you much of the information you will need to make this decision and will also help you determine if you are at risk of developing any of the serious side effects of the pill. It will tell you how to use the pill properly so that it will be as effective as possible. However, this leaflet is not a replacement for a careful discussion between you and your health-care provider. You should discuss the information provided in this leaflet with him or her, both when you first start taking the pill and during your revisits. You should also follow your health-care provider's advice with regard to regular check-ups while you are on the pill.

EFFECTIVENESS OF ORAL CONTRACEPTIVES

Oral contraceptives or "birth-control pills" or "the pill," are used to prevent pregnancy and are more effective than most other nonsurgical methods of birth control. When they are taken correctly, without missing any pills, the chance of becoming pregnant is approximately 1% per year (1 pregnancy per 100 women per year of use). Typical failure rates are approximately 5% per year (5 pregnancies per 100 women per year of use) when women who miss pills are included. The chance of becoming pregnant increases with each missed pill during each 28-day cycle of use.

In comparison, average failure rates for other methods of birth control during the first year of use are as follows:

IUD: 0.1-2% | Female condom alone: 21%
Depo-Provera® (injectable progestogen): 0.3% | Cervical cap
Norplant® System (levonorgestrel implants): 0.05% | Never given birth: 20%
Diaphragm with spermicides: 20% | Given birth: 40%
Spermicides alone: 26% | Periodic abstinence: 25%
Male condom alone: 14% | No methods: 85%

WHO SHOULD NOT TAKE ORAL CONTRACEPTIVES

Cigarette smoking increases the risk of serious adverse effects on the heart and blood vessels from oral-contraceptive use. This risk increases with age and with the amount of smoking (15 or more cigarettes per day has been associated with a significantly increased risk) and is quite marked in women over 35 years of age. Women who use oral contraceptives should not smoke.

Some women should not use the pill. For example, you should not take the pill if you have any of the following conditions:

- History of heart attack or stroke.
- Blood clots in the legs (thrombophlebitis), lungs (pulmonary embolism), or eyes.
- A history of blood clots in the deep veins of your legs.
- Chest pain (angina pectoris).
- Known or suspected breast cancer or cancer of the lining of the uterus, cervix or vagina, or certain hormonally-sensitive cancers.
- Unexplained vaginal bleeding (until a diagnosis is reached by your health-care provider).
- Liver tumor (benign or cancerous) or active liver disease.
- Take any Hepatitis C drug combination containing ombitasvir/paritaprevir/ritonavir, with or without dasabuvir. This may increase levels of the liver enzyme "alanine aminotransferase" (ALT) in the blood.
- Yellowing of the whites of the eyes or of the skin (jaundice) during pregnancy or during previous use of the pill.
- Known or suspected pregnancy.
- A need for surgery with prolonged bedrest.
- Heart valve or heart rhythm disorders that may be associated with formation of blood clots.
- Diabetes affecting your circulation.
- Headaches with neurological symptoms.
- Uncontrolled high blood pressure.
- Allergy or hypersensitivity to any of the components of levonorgestrel and ethinyl estradiol tablets.

Tell your health-care provider if you have had any of these conditions. Your health-care provider can recommend another method of birth control.

OTHER CONSIDERATIONS BEFORE TAKING ORAL CONTRACEPTIVES

Tell your health-care provider if you or any family member has ever had:

- Breast nodules, fibrocystic disease of the breast, an abnormal breast X-ray or mammogram.
- Diabetes.
- Elevated cholesterol or triglycerides.
- High blood pressure.
- A tendency to form blood clots.
- Migraine or other headaches or epilepsy.
- Depression.
- Gallbladder, liver, heart, or kidney disease.
- History of scanty or irregular menstrual periods.

Women with any of these conditions should be checked often by their health-care provider if they choose to use oral contraceptives. Also, be sure to inform your health-care provider if you smoke or are on any medications.

Although cardiovascular disease risks may be increased with oral contraceptive use in healthy, non-smoking women over 40 (even with the newer low-dose formulations), there are also greater potential health risks associated with pregnancy in older women.

RISKS OF TAKING ORAL CONTRACEPTIVES

1. Risks Of Developing Blood Clots

Blood clots and blockage of blood vessels are the most serious side effects of taking oral contraceptives and can cause death or serious disability. In particular, a clot in the legs can cause thrombophlebitis and a clot that travels to the lungs can cause a sudden blocking of the vessel carrying blood to the lungs. Rarely, clots occur in the blood vessels of the eye and may cause blindness, double vision, or impaired vision.

Users of combination oral contraceptives have a higher risk of developing blood clots compared to non-users. This risk is highest during the first year of combination oral-contraceptive use.

If you take oral contraceptives and need elective surgery, need to stay in bed for a prolonged illness or injury, or have recently delivered a baby, you may be at risk of developing blood clots. You should consult your health-care provider about stopping oral contraceptives three to four weeks before surgery and not taking oral contraceptives for two weeks after surgery or during bed rest. You should also not take oral contraceptives soon after delivery of a baby or after a midtrimester pregnancy termination. It is advisable to wait for at least four weeks after delivery if you are not breast-feeding. If you are breast-feeding, you should wait until you have weaned your child before using the pill. (See also the section While breast-feeding in GENERAL PRECAUTIONS.)

The risk of blood clots is greater in users of combination oral contraceptives compared to nonusers. This risk may be higher in users of high-dose pills (those containing 50 mcg or more of estrogen) and may also be greater with longer use. In addition, some of these increased risks may continue for a number of years after stopping combination oral contraceptives. The risk of abnormal blood clotting increases with age in both users and nonusers of combination oral contraceptives, but the increased risk from the oral contraceptive appears to be present at all ages.

The excess risk of blood clots is highest during the first year a woman ever uses a combined oral contraceptive. This increased risk is lower than blood clots associated with pregnancy. The use of combination oral contraceptives also increases the risk of other clotting disorders, including heart attack and stroke. Blood clots in veins cause death in 1% to 2% of cases. The risk of clotting is further increased in women with other conditions. Examples include: smoking, high blood pressure, abnormal lipid levels, certain inherited or acquired clotting disorders, obesity, surgery or injury, recent delivery or second trimester abortion, prolonged inactivity or bedrest. If possible, combination oral contraceptives should be stopped before surgery and during prolonged inactivity or bedrest.

Cigarette smoking increases the risk of serious cardiovascular events. This risk increases with age and amount of smoking and is quite pronounced in women over 35. Women who use combination oral contraceptives should be strongly advised not to smoke. If you smoke you should talk to your health care professional before taking combination oral contraceptives.

2. Heart Attacks And Strokes

Oral contraceptives may increase the tendency to develop strokes or transient ischemic attacks (blockage or rupture of blood vessels in the brain) and angina pectoris and heart attacks (blockage of blood vessels in the heart). Any of these conditions can cause death or serious disability.

Smoking greatly increases the possibility of suffering heart attacks and strokes. Furthermore, smoking and the use of oral contraceptives greatly increase the chances of developing and dying of heart disease.

Women with migraine (especially migraine/headache with neurological symptoms) who take oral contraceptives also may be at higher risk of stroke and must not use combination oral contraceptives (see section WHO SHOULD NOT TAKE ORAL CONTRACEPTIVES).

3. Gallbladder Disease

Oral-contraceptive users probably have a greater risk than nonusers of having gallbladder disease, although this risk may be related to pills containing high doses of estrogens. Oral-contraceptives may worsen existing gallbladder disease or accelerate the development of gallbladder disease in women previously without symptoms.

4. Liver Tumors

In rare cases, oral contraceptives can cause benign but dangerous liver tumors. These benign liver tumors can rupture and cause fatal internal bleeding. In addition, a possible but not definite association has been found with the pill and liver cancers in two studies in which a few women who developed these very rare cancers were found to have used oral contraceptives for long periods. However, liver cancers are extremely rare. The chance of developing liver cancer from using the pill is thus even rarer.

5. Risk of Cancer

It is not known if hormonal birth control pills causes breast cancer. Some studies, but not all, suggest that there could be a slight increase in the risk of breast cancer among current users with longer duration of use.

If you have breast cancer now, or have had it in the past, do not use hormonal birth control because some breast cancers are sensitive to hormones.

Some studies have found an increase in the incidence of cancer of the cervix in women who use oral contraceptives. However, this finding may be related to factors other than the use of oral contraceptives.

6. Lipid Metabolism And Pancreatitis

There have been reports of increases of blood cholesterol and triglycerides in users of combination oral contraceptives. Increases in triglycerides have led to inflammation of the pancreas (pancreatitis) in some cases.

ESTIMATED RISK OF DEATH FROM A BIRTH-CONTROL METHOD OR PREGNANCY

All methods of birth control and pregnancy are associated with a risk of developing certain diseases which may lead to disability or death. An estimate of the number of deaths associated with different methods of birth control and pregnancy has been calculated and is shown in the following table.

ANNUAL NUMBER OF BIRTH-RELATED OR METHOD-RELATED DEATHS ASSOCIATED WITH CONTROL OF FERTILITY PER 100,000 NONSTERILE WOMEN, BY FERTILITY-CONTROL METHOD AND ACCORDING TO AGE
Header$Method of control and outcome | 15–19 | 20–24 | 25–29 | 30–34 | 35–39 | 40–44
No fertility-control methods [Deaths are birth related] | 7.0 | 7.4 | 9.1 | 14.8 | 25.7 | 28.2
Oral contraceptives
nonsmoker [Deaths are method related] | 0.3 | 0.5 | 0.9 | 1.9 | 13.8 | 31.6
Oral contraceptives
Smoker | 2.2 | 3.4 | 6.6 | 13.5 | 51.1 | 117.2
IUD | 0.8 | 0.8 | 1.0 | 1.0 | 1.4 | 1.4
Condom | 1.1 | 1.6 | 0.7 | 0.2 | 0.3 | 0.4
Diaphragm/spermicide | 1.9 | 1.2 | 1.2 | 1.3 | 2.2 | 2.8
Periodic abstinence | 2.5 | 1.6 | 1.6 | 1.7 | 2.9 | 3.6

In the above table, the risk of death from any birth-control method is less than the risk of childbirth, except for oral-contraceptive users over the age of 35 who smoke and pill users over the age of 40 even if they do not smoke. It can be seen in the table that for women aged 15 to 39, the risk of death was highest with pregnancy (7 to 26 deaths per 100,000 women, depending on age). Among pill users who do not smoke, the risk of death was always lower than that associated with pregnancy for any age group, except for those women over the age of 40, when the risk increases to 32 deaths per 100,000 women, compared to 28 associated with pregnancy at that age. However, for pill users who smoke and are over the age of 35, the estimated number of deaths exceeds those for other methods of birth control. If a woman is over the age of 40 and smokes, her estimated risk of death is four times higher (117/100,000 women) than the estimated risk associated with pregnancy (28/100,000 women) in that age group.

The suggestion that women over 40 who do not smoke should not take oral contraceptives is based on information from older high-dose pills. An Advisory Committee of the FDA discussed this issue in 1989 and recommended that the benefits of oral-contraceptive use by healthy, nonsmoking women over 40 years of age may outweigh the possible risks. Older women, as all women, who take oral contraceptives, should take an oral contraceptive which contains the least amount of estrogen and progestogen that is compatible with the individual patient needs.

WARNING SIGNALS

If any of these adverse effects occur while you are taking oral contraceptives, call your health-care provider immediately:

- Sharp chest pain, coughing of blood, or sudden shortness of breath (indicating a possible clot in the lung).
- Pain in the calf (indicating a possible clot in the leg).
- Crushing chest pain or heaviness in the chest (indicating a possible heart attack).
- Sudden severe headache or vomiting, dizziness or fainting, disturbances of vision or speech, weakness, or numbness in an arm or leg (indicating a possible stroke).
- Sudden partial or complete loss of vision (indicating a possible clot in the eye).
- Breast lumps (indicating possible breast cancer or fibrocystic disease of the breast; ask your health-care provider to show you how to examine your breasts).
- Severe pain or tenderness in the stomach area (indicating a possibly ruptured liver tumor).
- Difficulty in sleeping, weakness, lack of energy, fatigue, or change in mood (possibly indicating severe depression).
- Jaundice or a yellowing of the skin or eyeballs, accompanied frequently by fever, fatigue, loss of appetite, dark-colored urine, or light-colored bowel movements (indicating possible liver problems).

SIDE EFFECTS OF ORAL CONTRACEPTIVES

1. Unscheduled or Breakthrough Vaginal Bleeding Or Spotting

Unscheduled vaginal bleeding or spotting may occur while you are taking the pills. Unscheduled bleeding may vary from slight staining between menstrual periods to breakthrough bleeding which is a flow much like a regular period. Unscheduled bleeding occurs most often during the first few months of oral-contraceptive use, but may also occur after you have been taking the pill for some time. Such bleeding may be temporary and usually does not indicate any serious problems. It is important to continue taking your pills on schedule. If the bleeding occurs in more than one cycle or lasts for more than a few days, talk to your health-care provider.

2. Contact Lenses

If you wear contact lenses and notice a change in vision or an inability to wear your lenses, contact your health-care provider.

3. Fluid Retention

Oral contraceptives may cause edema (fluid retention) with swelling of the fingers or ankles and may raise your blood pressure. If you experience fluid retention, contact your health-care provider.

4. Melasma

A spotty darkening of the skin is possible, particularly of the face.

5. Other Side Effects

Other side effects may include nausea, breast tenderness, change in appetite, headache, nervousness, depression, dizziness, loss of scalp hair, rash, vaginal infections, inflammation of the pancreas, and allergic reactions.

If any of these side effects bother you, call your health-care provider.

GENERAL PRECAUTIONS

1. Missed Periods And Use Of Oral Contraceptives Before Or During Early Pregnancy

There may be times when you may not menstruate regularly after you have completed taking a cycle of pills. If you have taken your pills regularly and miss one menstrual period, continue taking your pills for the next cycle but be sure to inform your health-care provider before doing so. If you have not taken the pills daily as instructed and missed a menstrual period, or if you missed two consecutive menstrual periods, you may be pregnant. Check with your health-care provider immediately to determine whether you are pregnant. Stop taking oral contraceptives if you are pregnant.

There is no conclusive evidence that oral-contraceptive use is associated with an increase in birth defects, when taken inadvertently during early pregnancy. Previously, a few studies had reported that oral contraceptives might be associated with birth defects, but these studies have not been confirmed. Nevertheless, oral contraceptives should not be used during pregnancy. You should check with your health-care provider about risks to your unborn child of any medication taken during pregnancy.

2. While Breast-Feeding

If you are breast-feeding, consult your health-care provider before starting oral contraceptives. Some of the drug will be passed on to the child in the milk. A few adverse effects on the child have been reported, including yellowing of the skin (jaundice) and breast enlargement. In addition, oral contraceptives may decrease the amount and quality of your milk. If possible, do not use oral contraceptives while breast-feeding. You should use another method of contraception since breast-feeding provides only partial protection from becoming pregnant and this partial protection decreases significantly as you breast-feed for longer periods of time. You should consider starting oral contraceptives only after you have weaned your child completely.

3. Laboratory Tests

If you are scheduled for any laboratory tests, tell your doctor you are taking birth-control pills. Certain blood tests may be affected by birth-control pills.

4. Drug Interactions

Certain drugs may interact with birth-control pills to make them less effective in preventing pregnancy or cause an increase in breakthrough bleeding. Such drugs include rifampin, drugs used for epilepsy such as barbiturates (for example, phenobarbital) and phenytoin (Dilantin® is one brand of this drug), primidone (Mysoline®), topiramate (Topamax®), carbamazepine (Tegretol® is one brand of this drug), phenylbutazone (Butazolidin® is one brand), some drugs used for HIV or AIDS such as ritonavir (Norvir®), modafinil (Provigil®) and possibly certain antibiotics (such as ampicillin and other penicillins, and tetracyclines), and herbal products containing St. John's Wort (Hypericum perforatum). You may also need to use a nonhormonal method of contraception during any cycle in which you take drugs that can make oral contraceptives less effective.

You may be at higher risk of a specific type of liver dysfunction if you take troleandomycin and oral contraceptives at the same time.

You should inform your health-care provider about all medicines you are taking, including nonprescription products.

5. Sexually Transmitted Diseases

This product (like all oral contraceptives) is intended to prevent pregnancy. It does not protect against transmission of HIV (AIDS) and other sexually transmitted diseases such as chlamydia, genital herpes, genital warts, gonorrhea, hepatitis B, and syphilis.

HOW TO TAKE LEVONORGESTREL AND ETHINYL ESTRADIOL TABLETS

IMPORTANT POINTS TO REMEMBER

BEFORE YOU START TAKING LEVONORGESTREL AND ETHINYL ESTRADIOL TABLETS:

1. BE SURE TO READ THESE DIRECTIONS:

Before you start taking levonorgestrel and ethinyl estradiol tablets.

And

Anytime you are not sure what to do.

2. THE RIGHT WAY TO TAKE THE PILL IS TO TAKE ONE PILL EVERY DAY AT THE SAME TIME.

If you miss pills you could get pregnant. This includes starting the pack late. The more pills you miss, the more likely you are to get pregnant. See "WHAT TO DO IF YOU MISS PILLS" below.

3. MANY WOMEN HAVE SPOTTING OR LIGHT BLEEDING, OR MAY FEEL SICK TO THEIR STOMACH DURING THE FIRST 1-3 PACKS OF PILLS.

If you feel sick to your stomach, do not stop taking levonorgestrel and ethinyl estradiol tablets. The problem will usually go away. If it doesn't go away, check with your health-care provider.

4. MISSING PILLS CAN ALSO CAUSE SPOTTING OR LIGHT BLEEDING, even when you make up these missed pills.

On the days you take 2 pills to make up for missed pills, you could also feel a little sick to your stomach.

5. IF YOU HAVE VOMITING (within 4 hours after you take your pill), you should follow the instructions for WHAT TO DO IF YOU MISS PILLS. IF YOU HAVE DIARRHEA or IF YOU TAKE SOME MEDICINES, including some antibiotics, your pills may not work as well.

Use a back-up nonhormonal method (such as condoms or spermicide) until you check with your health-care provider.

6. IF YOU HAVE TROUBLE REMEMBERING TO TAKE THE PILL, talk to your health-care provider about how to make pill-taking easier or about using another method of birth control.

7. IF YOU HAVE ANY QUESTIONS OR ARE UNSURE ABOUT THE INFORMATION IN THIS LEAFLET, contact your health-care provider.

BEFORE YOU START TAKING LEVONORGESTREL AND ETHINYL ESTRADIOL TABLETS

1. DECIDE WHAT TIME OF DAY YOU WANT TO TAKE YOUR PILL. It is important to take it at about the same time every day.

2. LOOK AT YOUR PILL PACK.

The pill pack has 21 "active" white pills (with hormones) to take for 3 weeks, followed by 1 week of reminder orange pills (without hormones).

3. FIND:

1. where on the pack to start taking pills, and

2. in what order to take the pills (follow the arrow).

4. BE SURE YOU HAVE READY AT ALL TIMES:

ANOTHER KIND OF BIRTH CONTROL (such as condoms or spermicide) to use as a back-up in case you miss pills.

AN EXTRA, FULL PILL PACK.

* For use of day labels, see WHEN TO START THE FIRST PACK OF PILLS below

WHEN TO START THE FIRST PACK OF PILLS

You have a choice of which day to start taking your first pack of pills.

Decide with your health-care provider which is the best day for you. Pick a time of day which will be easy to remember.

DAY 1 START

1. Take the first "active" white pill of the first pack during the first 24 hours of your period.
2. You will not need to use a back-up nonhormonal method of birth control, since you are starting the pill at the beginning of your period.

SUNDAY START

1. Take the first "active" white pill of the first pack on the Sunday after your period starts, even if you are still bleeding. If your period begins on Sunday, start the pack that same day.
2. Use a nonhormonal method of birth control (such as condoms or spermicide) as a backup method if you have sex anytime from the Sunday you start your first pack until the next Sunday (7 days).

WHAT TO DO DURING THE MONTH

1. Take one pill at the same time every day until the pack is empty.

Do not skip pills even if you are spotting or bleeding between monthly periods or feel sick to your stomach (nausea).

Do not skip pills even if you do not have sex very often.

2. When you finish a pack:

Start the next pack on the day after your last "reminder" pill. Do not wait any days between packs.

IF YOU SWITCH FROM ANOTHER BRAND OF COMBINATION PILLS

If your previous brand had 21 pills: Wait 7 days to start taking levonorgestrel and ethinyl estradiol tablets. You will probably have your period during that week. Be sure that no more than 7 days pass between the 21-day pack and taking the first white levonorgestrel and ethinyl estradiol tablets ("active" with hormone).

If your previous brand had 28 pills: Start taking the first white levonorgestrel and ethinyl estradiol tablets ("active" with hormone) on the day after your last reminder pill. Do not wait any days between packs.

WHAT TO DO IF YOU MISS PILLS

Levonorgestrel and ethinyl estradiol tablets may not be as effective if you miss white "active" pills, and particularly if you miss the first few or the last few white "active" pills in a pack.

If you MISS 1 white "active" pill:

1. Take it as soon as you remember. Take the next pill at your regular time. This means you may take 2 pills in 1 day.
2. You COULD BECOME PREGNANT if you have sex in the 7 days after you restart your pills. You MUST use a nonhormonal birth-control method (such as condoms or spermicide) as a back-up for those 7 days.

If you MISS 2 white "active" pills in a row in WEEK 1 OR WEEK 2 of your pack:

1. Take 2 pills on the day you remember and 2 pills the next day.
2. Then take 1 pill a day until you finish the pack.
3. You COULD BECOME PREGNANT if you have sex in the 7 days after you restart your pills. You MUST use a nonhormonal birth-control method (such as condoms or spermicide) as a back-up for those 7 days.

If you MISS 2 white "active" pills in a row in THE 3rd WEEK:

1. If you are a Day 1 Starter:

THROW OUT the rest of the pill pack and start a new pack that same day.

If you are a Sunday Starter:

Keep taking 1 pill every day until Sunday.

On Sunday, THROW OUT the rest of the pack and start a new pack of pills that same day.

2. You may not have your period this month but this is expected

However, if you miss your period 2 months in a row, call your health-care provider because you might be pregnant.

3. You COULD BECOME PREGNANT if you have sex in the 7 days after you restart yourpills. You MUST use a nonhormonal birth-control method (such as condoms orspermicide) as a back-up for those 7 days.

If you MISS 3 OR MORE white "active" pills in a row (during the first 3 weeks):

1. If you are a Day 1 Starter:

THROW OUT the rest of the pill pack and start a new pack that same day.

If you are a Sunday Starter:

Keep taking 1 pill every day until Sunday.

On Sunday, THROW OUT the rest of the pack and start a new pack of pills that same day.

2. You may not have your period this month but this is expected.

However, if you miss your period 2 months in a row, call your health-care provider because you might be pregnant.

3. You COULD BECOME PREGNANT if you have sex in the 7 days after you restart your pills.

You MUST use a nonhormonal birth-control method (such as condoms or spermicide) as a back-up for those 7 days.

If you forget any of the 7 orange "reminder" pills in Week 4:

THROW AWAY the pills you missed.

Keep taking 1 pill each day until the pack is empty.

You do not need a back-up nonhormonal birth-control method if you start your next pack on time.

FINALLY, IF YOU ARE STILL NOT SURE WHAT TO DO ABOUT THE PILLS YOU HAVE MISSED

Use a BACK-UP NONHORMONAL BIRTH-CONTROL METHOD anytime you have sex.

KEEP TAKING ONE PILL EACH DAY until you can reach your health-care provider.

PREGNANCY DUE TO PILL FAILURE

The incidence of pill failure resulting in pregnancy is approximately 1 per year (1 pregnancy per 100 women per year of use) if taken every day as directed, but the more typical failure rate is approximately 5% per year (5 pregnancies per 100 women per year of use) including women who do not always take the pill exactly as directed without missing any pills. If you do become pregnant, the risk to the fetus is minimal, but you should stop taking your pills and discuss the pregnancy with your health-care provider.

PREGNANCY AFTER STOPPING THE PILL

There may be some delay in becoming pregnant after you stop using oral contraceptives, especially if you had irregular menstrual cycles before you used oral contraceptives. It may be advisable to postpone conception until you begin menstruating regularly once you have stopped taking the pill and desire pregnancy.

There does not appear to be any increase in birth defects in newborn babies when pregnancy occurs soon after stopping the pill.

BIRTH CONTROL AFTER STOPPING THE PILL

If you do not wish to become pregnant after stopping the pill, you should use another method of birth control immediately after stopping levonorgestrel and ethinyl estradiol tablets. Speak to your health-care provider about another method of birth control.

OVERDOSAGE

Overdosage may cause nausea, vomiting, breast tenderness, dizziness, abdominal pain and fatigue/drowsiness. Withdrawal bleeding may occur in females. In case of overdosage, contact your health-care provider or pharmacist.

OTHER INFORMATION

Your health-care provider will take a medical and family history before prescribing oral contraceptives and will examine you. The physical examination may be delayed to another time if you request it and your health-care provider believes that it is appropriate to postpone it. You should be reexamined at least once a year. Be sure to inform your health-care provider if there is a family history of any of the conditions listed previously in this leaflet. Be sure to keep all appointments with your health-care provider, because this is a time to determine if there are early signs of side effects of oral-contraceptive use.

Do not use the drug for any condition other than the one for which it was prescribed. This drug has been prescribed specifically for you; do not give it to others who may want birth-control pills.

HEALTH BENEFITS FROM ORAL CONTRACEPTIVES

In addition to preventing pregnancy, use of oral contraceptives may provide certain benefits. They are:

- Menstrual cycles may become more regular.
- Blood flow during menstruation may be lighter, and less iron may be lost. Therefore, anemia due to iron deficiency is less likely to occur.
- Pain or other symptoms during menstruation may be encountered less frequently.
- Ovarian cysts may occur less frequently.
- Ectopic (tubal) pregnancy may occur less frequently.
- Noncancerous cysts or lumps in the breast may occur less frequently.
- Acute pelvic inflammatory disease may occur less frequently.
- Oral-contraceptive use may provide some protection against developing two forms of cancer: cancer of the ovaries and cancer of the lining of the uterus.

If you want more information about birth-control pills, ask your health-care provider or pharmacist. They have a more technical leaflet called the Professional Labeling which you may wish to read.

If you have any questions or want more information about levonorgestrel and ethinyl estradiol tablets, talk to your health-care provider or pharmacist, address medical queries to www.birthcontrolhealth.com or at 1-800-399-2561.

The brands listed are trademarks of their respective owners and are not trademarks of Lupin Pharmaceuticals, Inc. The makers of these brands are not affiliated with and do not endorse Lupin Pharmaceuticals, Inc. or its products.

Distributed by:

Lupin Pharmaceuticals, Inc.

Naples, FL 34108

United States

Manufactured by:

Lupin Limited

Pithampur (M.P.) - 454 775

INDIA

Revised: December 2024 ID#: 278044

PRINCIPAL DISPLAY PANEL

Levonorgestrel and Ethinyl Estradiol Tablets USP, 0.1 mg/0.02 mg

Rx Only

NDC 68180-854-71

Blister Label: 28 Tablets

Levonorgestrel and Ethinyl Estradiol Tablets USP, 0.1 mg/0.02 mg

Rx Only

NDC 68180-854-73

Carton Label: 3 Blisters of 28 Tablets Each